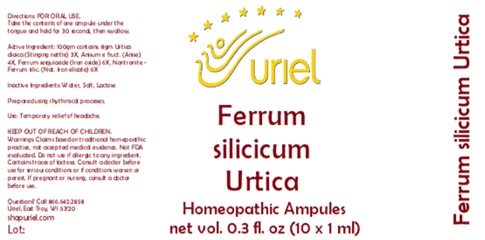 DRUG LABEL: Ferrum Silicicum Urtica
NDC: 48951-4176 | Form: LIQUID
Manufacturer: Uriel Pharmacy Inc.
Category: homeopathic | Type: HUMAN OTC DRUG LABEL
Date: 20250107

ACTIVE INGREDIENTS: ANISE 1 [hp_X]/1 mL; URTICA DIOICA 3 [hp_X]/1 mL; SILICON DIOXIDE 6 [hp_X]/1 mL; FERRIC OXIDE RED 6 [hp_X]/1 mL
INACTIVE INGREDIENTS: SODIUM CHLORIDE; WATER; LACTOSE, UNSPECIFIED FORM

Ferrum Silicicum Urtica

INDICATIONS AND USAGE

Directions: FOR ORAL USE.

DOSAGE AND ADMINISTRATION

Take the contents of one ampule under the tongue and hold for 30 seconds, then swallow.

Active Ingredient: Anisum (Anise) 1X, Urtica dioica (Stinging nettle) 3X, Ferrum sesquioxide (Iron oxide) 6X, Nontronite - Ferrum silic. (Nat. Iron silicate) 6X

Inactive Ingredients: Water, Salt, Lactose

Prepared using rhythmical processes.

PURPOSE

Use: Temporary relief of headache.

KEEP OUT OF REACH OF CHILDREN.

WARNINGS

Warnings: Claims based on traditional homepoathic practice, not accepted medical evidence. Not FDA evaluated. Do not use if allergic to any ingredient. Contains traces of lactose. Consult a doctor before use for serious conditions or if conditions worsen or persist. If pregnant or nursing, consult a doctor before use.

Questions? Call 866.642.2858
Uriel, East Troy, WI 53120
shopuriel.com Lot: